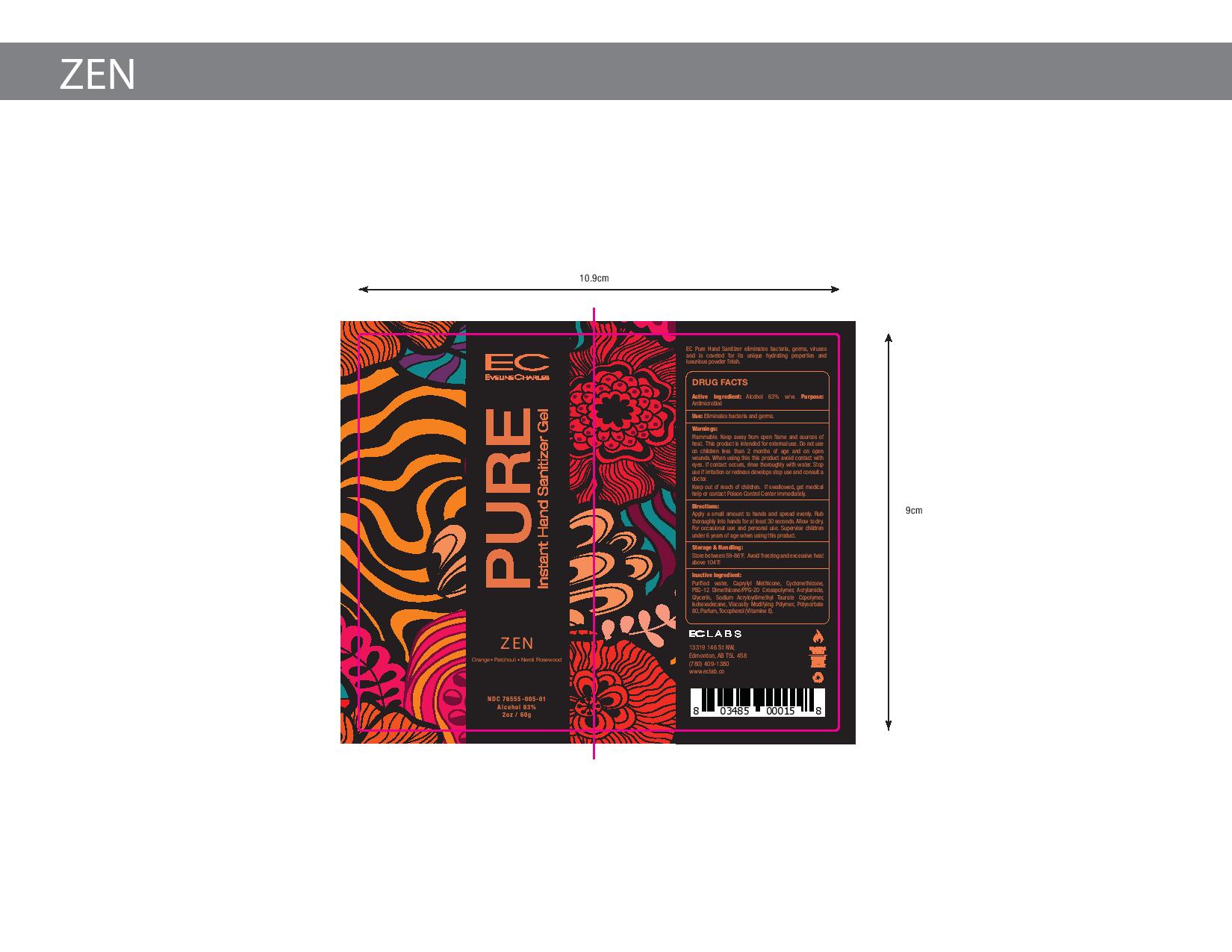 DRUG LABEL: EC Pure Instant Cream Hand Sanitizer Zen
NDC: 76555-005 | Form: CREAM
Manufacturer: Ec Labs Inc
Category: otc | Type: HUMAN OTC DRUG LABEL
Date: 20220114

ACTIVE INGREDIENTS: ALCOHOL 37.8 g/60 g
INACTIVE INGREDIENTS: AMMONIUM ACRYLOYLDIMETHYLTAURATE, DIMETHYLACRYLAMIDE, LAURYL METHACRYLATE AND LAURETH-4 METHACRYLATE COPOLYMER, TRIMETHYLOLPROPANE TRIACRYLATE CROSSLINKED (45000 MPA.S) 0.78 g/60 g; MANDARIN OIL 0.0048 g/60 g; ORANGE OIL 0.0744 g/60 g; LEMON OIL 0.0036 g/60 g; CYCLOMETHICONE 1.02 g/60 g; PEG/PPG-18/12 DIMETHICONE 5.1 g/60 g; SODIUM ACRYLOYLDIMETHYLTAURATE 1.74 g/60 g; LAVENDER OIL 0.00132 g/60 g; POGOSTEMON CABLIN LEAF OIL 0.0064 g/60 g; CITRUS NOBILIS 0.0024 g/60 g; GLYCERIN 0.3 g/60 g; TOCOPHEROL 0.06 g/60 g; WATER 13.09 g/60 g; ROSEWOOD OIL 0.00192 g/60 g; CITRUS AURANTIUM FLOWER OIL 0.0064 g/60 g

Eveline Charles Pure Instant Cream Hand Sanitizer Zen

This is a hand sanitizer manufactured according to the Temporary Policy for Preparation of Certain Alcohol-Based Hand Sanitizer Products During the Public Health Emergency (CoViD-19); Guidance for Industry.

The hand sanitizer is manufactured using only the following United States Pharmacopoeia (USP) grade ingredients in the preparation of the product (percentage in final product formulation) consistent with World Health Organization (WHO) recommendations:

1. Alcohol (ethanol) (USP or Food Chemical Codex (FCC) grade) (80%, volume/volume (v/v)) in an aqueous solution denatured according to Alcohol and Tobacco Tax and Trade Bureau regulations in 27 CFR part 20.
2. Glycerol (1.45% v/v).
3. Hydrogen peroxide (0.125% v/v).
4. Sterile distilled water or boiled cold water.

The firm does not add other active or inactive ingredients. Different or additional ingredients may impact the quality and potency of the product.

Active Ingredient(s)

Alcohol 63% w/w. Purpose: Antimicrobial

Purpose

Antimicrobial, Hand Sanitizer

Use

Eliminates bacteria and germs.

Warnings

Flammable. Keep away from open flame and sources of heat. This product is intended for external use only.

Do not use iin children less than 2 months of age and on open wounds.

When using this product avoid contact with eyes. If contact occurs, rinse thoroughly with water.

Stop use if irritation or redness develops and consult a doctor.

Keep out of reach of children. If swallowed, get medical help or contact a Poison Control Center right away.

Directions

Apply a small amount to hands and spread evenly.

Rub thoroughly into hands for at lease 30 secconds.

Allow to dry.

For occasional and personal use.

Superrvise children under 6 years of age when using this product.

Other information

- Store between 59-86F
- Avoid freezing and excessive heat above104F

Inactive ingredients

glycerin, hydrogen peroxide, purified water USP

Package Label - Principal Display Panel

60g NDC:76555-005-01